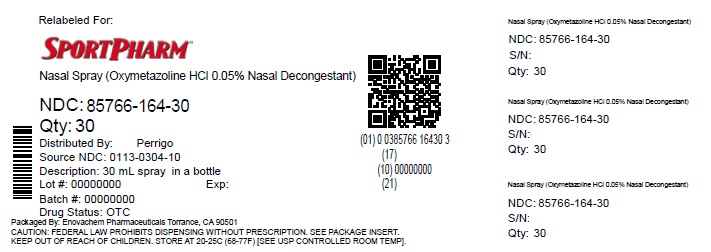 DRUG LABEL: Good Sense Nasal
NDC: 85766-164 | Form: SPRAY
Manufacturer: Sportpharm LLC
Category: otc | Type: HUMAN OTC DRUG LABEL
Date: 20260206

ACTIVE INGREDIENTS: OXYMETAZOLINE HYDROCHLORIDE 0.5 mg/1 mL
INACTIVE INGREDIENTS: BENZALKONIUM CHLORIDE; BENZYL ALCOHOL; SODIUM PHOSPHATE, DIBASIC, UNSPECIFIED FORM; EDETATE DISODIUM; SODIUM PHOSPHATE, MONOBASIC, UNSPECIFIED FORM; POLYETHYLENE GLYCOL, UNSPECIFIED; POVIDONE, UNSPECIFIED; PROPYLENE GLYCOL; WATER

Perrigo Nasal Spray Drug Facts

Active ingredient

Oxymetazoline hydrochloride 0.05%

Purpose

Nasal decongestant

Uses

- temporarily relieves nasal congestion due to:
  - common cold
  - hay fever
  - upper respiratory allergies
- temporarily relieves sinus congestion and pressure
- shrinks swollen nasal membranes so you can breathe more freely

Warnings

Ask a doctor before use if you have

- heart disease
- high blood pressure
- thyroid disease
- diabetes
- trouble urinating due to an enlarged prostate gland

When using this product

- do not use more than directed
- do not use for more than 3 days. Use only as directed. Frequent or prolonged use may cause nasal congestion to recur or worsen.
- temporary discomfort such as burning, stinging, sneezing or an increase in nasal discharge may occur
- use of this container by more than one person may spread infection

Stop use and ask a doctor if

symptoms persist

If pregnant or breast-feeding,

ask a health professional before use.

Keep out of reach of children.

If swallowed, get medical help or contact a Poison Control Center right away (1-800-222-1222).

Directions

- adults and children 6 to under 12 years of age (with adult supervision): 2 or 3 sprays in each nostril not more often than every 10 to 12 hours. Do not exceed 2 doses in any 24-hour period.
- children under 6 years of age: ask a doctor

To Use: Push firmly down on cap and turn counter clockwise. To spray, squeeze bottle quickly and firmly. Do not tilt head backward while spraying. Wipe nozzle clean after use. Secure cap after use.

Other information

- store at 20-25°C (68-77°F)
- retain carton for future reference on full labeling

Inactive ingredients

benzalkonium chloride solution, benzyl alcohol, dibasic sodium phosphate, edetate disodium, monobasic sodium phosphate, polyethylene glycol, povidone, propylene glycol, purified water

Questions or comments?

1-800-719-9260